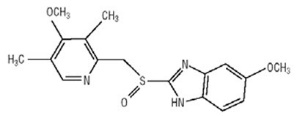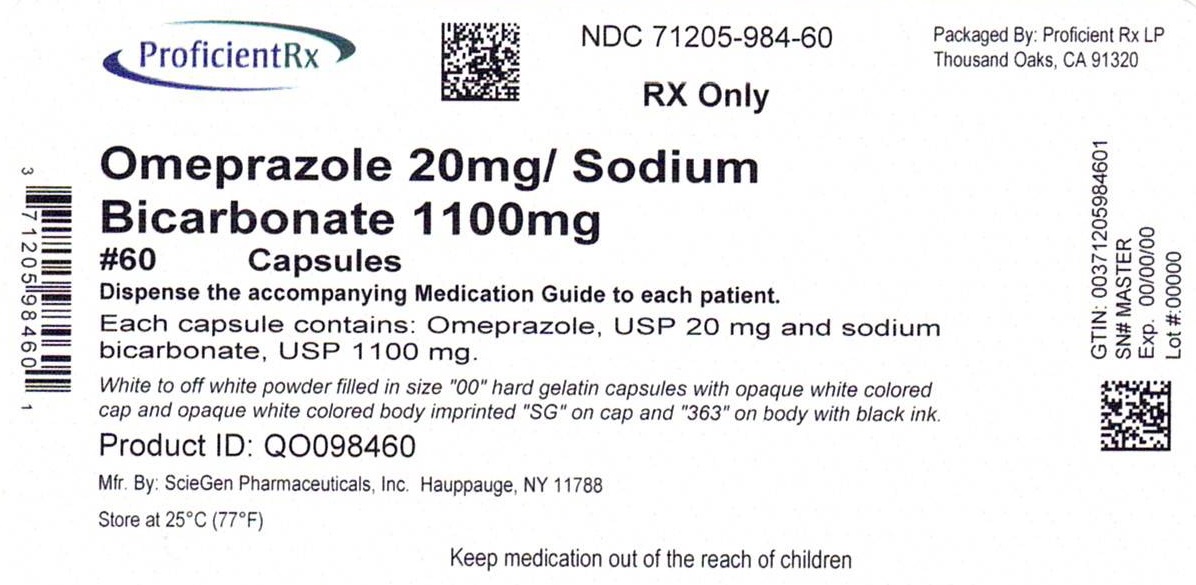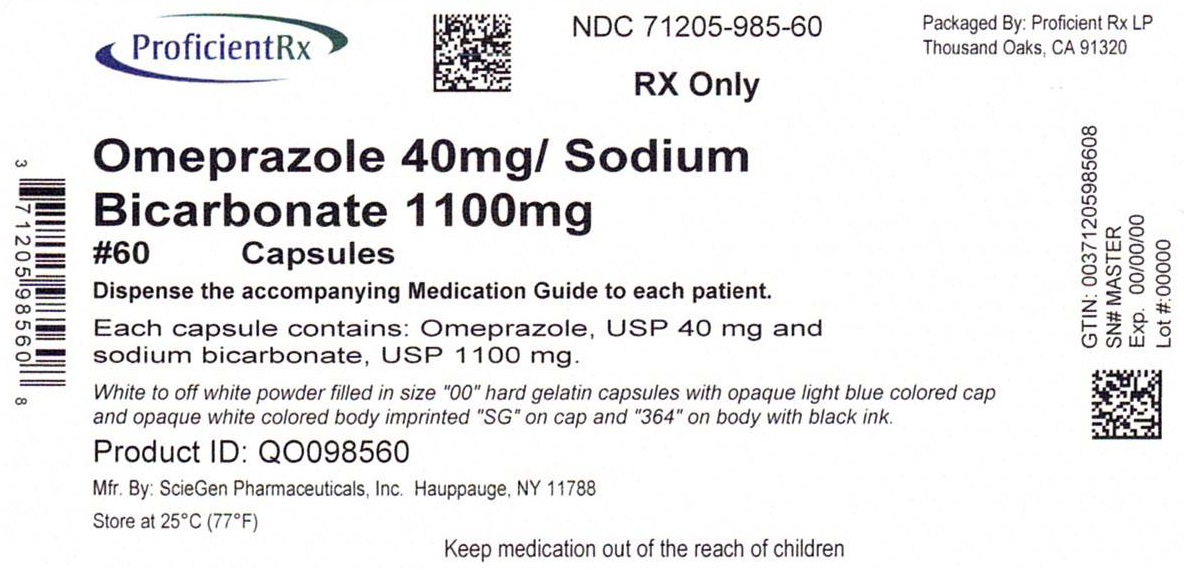 DRUG LABEL: Omeprazole/Bicarbonate
NDC: 71205-984 | Form: CAPSULE, GELATIN COATED
Manufacturer: Proficient Rx LP
Category: prescription | Type: HUMAN PRESCRIPTION DRUG LABEL
Date: 20230201

ACTIVE INGREDIENTS: Omeprazole 20 mg/1 1; Sodium Bicarbonate 1100 mg/1 1
INACTIVE INGREDIENTS: CROSCARMELLOSE SODIUM; SODIUM STEARYL FUMARATE; GELATIN, UNSPECIFIED; SODIUM LAURYL SULFATE; FERROSOFERRIC OXIDE; PROPYLENE GLYCOL; BUTYL ALCOHOL; TITANIUM DIOXIDE; ALCOHOL; ISOPROPYL ALCOHOL; POTASSIUM HYDROXIDE; SHELLAC; AMMONIA

HIGHLIGHTS OF PRESCRIBING INFORMATION

These highlights do not include all the information needed to use OMEPRAZOLE AND SODIUM BICARBONATE CAPSULES safely and effectively. See full prescribing information for OMEPRAZOLE AND SODIUM BICARBONATE CAPSULES.
OMEPRAZOLE and SODIUM BICARBONATE capsules, for oral use
Initial U.S. Approval: 2004

RECENT MAJOR CHANGES

Warnings and Precautions, Fundic Gland Polyps (5.13) | 06/2018

1 INDICATIONS AND USAGE

Omeprazole and sodium bicarbonate is a proton pump inhibitor (PPI) indicated for:

- Short-term treatment of active duodenal ulcer (1.1)
- Short-term treatment of active benign gastric ulcer (1.2)
- Treatment of gastroesophageal reflux disease (GERD) (1.3)
- Maintenance of healing of erosive esophagitis (1.4)

The safety and effectiveness of omeprazole and sodium bicarbonate capsules in pediatric patients (<18 years of age) have not been established. (8.4)

2 DOSAGE AND ADMINISTRATION

- Short-Term Treatment of Active Duodenal Ulcer: 20 mg once daily for 4 weeks (some patients may require an additional 4 weeks of therapy (14.1)) (2)
- Gastric Ulcer: 40 mg once daily for 4-8 weeks (2)
- Gastroesophageal Reflux Disease (GERD) (2)
  - Symptomatic GERD (with no esophageal erosions): 20 mg once daily for up to 4 weeks
  - Erosive Esophagitis: 20 mg once daily for 4-8 weeks
- Maintenance of Healing of Erosive Esophagitis: 20 mg once daily* (2)

*Studied for 12 months

3 DOSAGE FORMS AND STRENGTHS

- Omeprazole and sodium bicarbonate is available as a capsule in 20 mg and 40 mg strengths. (3)

4 CONTRAINDICATIONS

- Known hypersensitivity to any components of the formulation (4)

5 WARNINGS AND PRECAUTIONS

- Gastric Malignancy: In adults, symptomatic response does not preclude the presence of gastric malignancy. Consider additional follow-up and diagnostic testing. (5.1)
- Acute interstitial nephritis has been observed in patients taking PPIs. (5.2)
- Buffer Content: contains sodium bicarbonate (5.3)
- PPI therapy may be associated with increased risk of Clostridium difficile-associated diarrhea. (5.4)
- Bone Fracture: Long-term and multiple daily dose PPI therapy may be associated with an increased risk for osteoporosis-related fractures of the hip, wrist, or spine. (5.5)
- Cutaneous and Systemic Lupus Erythematosus: Mostly cutaneous; new onset or exacerbation of existing disease; discontinue omeprazole and sodium bicarbonate and refer to specialist for evaluation. (5.6)
- Avoid concomitant use of omeprazole and sodium bicarbonate with clopidogrel. (5.7)
- Cyanocobalamin (Vitamin B-12) Deficiency: Daily long-term use (e.g., longer than 3 years) may lead to malabsorption or a deficiency of cyanocobalamin. (5.8)
- Hypomagnesemia has been reported rarely with prolonged treatment with PPIs. (5.9)
- Avoid concomitant use of omeprazole and sodium bicarbonate with St. John's Wort or rifampin due to the potential reduction in omeprazole concentrations. (5.10, 7.2)
- Interactions with Diagnostic Investigations for Neuroendocrine Tumors: Increases in intragastric pH may result in hypergastrinemia and enterochromaffin-like cell hyperplasia and increased Chromogranin A levels which may interfere with diagnostic investigations for neuroendocrine tumors. (5.11, 12.2)
- Interaction with Methotrexate: Concomitant use with PPIs may elevate and/or prolong serum concentrations of methotrexate and/or its metabolite, possibly leading to toxicity. With high dose methotrexate administration, consider a temporary withdrawal of omeprazole and sodium bicarbonate. (5.12, 7.8)
- Fundic Gland Polyps: Risk increases with long-term use, especially beyond one year. Use the shortest duration of therapy. (5.13)

6 ADVERSE REACTIONS

Most common adverse reactions (incidence ≥ 2%) are: headache, abdominal pain, nausea, diarrhea, vomiting, and flatulence (6)

To report SUSPECTED ADVERSE REACTIONS, contact Westminster Pharmaceuticals, LLC at 1-844-221-7294 or FDA at 1-800-FDA-1088 or www.fda.gov/medwatch.

7 DRUG INTERACTIONS

- May interfere with drugs for which gastric pH can affect bioavailability (e.g., ketoconazole, ampicillin esters, iron salts, erlotinib, digoxin, and mycophenolate mofetil). (7.1)
- Drugs metabolized by cytochrome P450 (e.g., diazepam, warfarin, phenytoin, cyclosporine, disulfiram, benzodiazepines): Omeprazole and sodium bicarbonate can prolong their elimination. Monitor to determine the need for possible dose adjustments when taken with omeprazole and sodium bicarbonate. (7.2)
- Patients treated with proton pump inhibitors and warfarin concomitantly may need to be monitored for increases in INR and prothrombin time. (7.2)
- Voriconazole: May increase plasma levels of omeprazole. (7.2)
- Saquinavir: Omeprazole and sodium bicarbonate increases plasma levels of saquinavir. (7.3)
- Omeprazole and sodium bicarbonate may reduce plasma levels of atazanavir and nelfinavir. (7.3)
- Clopidogrel: Omeprazole and sodium bicarbonate decreases exposure to the active metabolite of clopidogrel. (7.5)
- Tacrolimus: Omeprazole and sodium bicarbonate may increase serum levels of tacrolimus. (7.6)

8 USE IN SPECIFIC POPULATIONS

- Pregnancy: Based upon animal data, may cause fetal harm. (8.1)
- The safety and effectiveness of omeprazole and sodium bicarbonate in pediatric patients less than 18 years of age have not been established. (8.4)
- Hepatic Impairment: Consider dose reduction, particularly for maintenance of healing of erosive esophagitis. (12.3)

FULL PRESCRIBING INFORMATION

1 INDICATIONS AND USAGE

1.1 Duodenal Ulcer

Omeprazole and sodium bicarbonate is indicated for short-term treatment of active duodenal ulcer. Most patients heal within four weeks. Some patients may require an additional four weeks of therapy. [See Clinical Studies (14.1).]

1.2 Gastric Ulcer

Omeprazole and sodium bicarbonate is indicated for short-term treatment (4-8 weeks) of active benign gastric ulcer. [See Clinical Studies (14.2).]

1.3 Treatment of Gastroesophageal Reflux Disease (GERD)

Symptomatic GERD

Omeprazole and sodium bicarbonate is indicated for the treatment of heartburn and other symptoms associated with GERD for up to 4 weeks. [See Clinical Studies (14.3).]

Erosive Esophagitis

Omeprazole and sodium bicarbonate is indicated for the short-term treatment (4-8 weeks) of erosive esophagitis which has been diagnosed by endoscopy.

The efficacy of omeprazole and sodium bicarbonate used for longer than 8 weeks in these patients has not been established. If a patient does not respond to 8 weeks of treatment, it may be helpful to give up to an additional 4 weeks of treatment. If there is recurrence of erosive esophagitis or GERD symptoms (e.g., heartburn), an additional 4-8 week courses of omeprazole and sodium bicarbonate may be considered. [See Clinical Studies (14.3).]

1.4 Maintenance of Healing of Erosive Esophagitis

Omeprazole and sodium bicarbonate is indicated to maintain healing of erosive esophagitis. Controlled studies do not extend beyond 12 months. [See Clinical Studies (14.4).]

2 DOSAGE AND ADMINISTRATION

Omeprazole and sodium bicarbonate is available as a capsule in 20 mg and 40 mg strengths of omeprazole for adult use. Directions for use for each indication are summarized in Table 1. All recommended doses throughout the labeling are based upon omeprazole.

Since both the 20 mg and 40 mg capsules contain the same amount of sodium bicarbonate (1,100 mg), two capsules of 20 mg are not equivalent to one capsule of omeprazole and sodium bicarbonate 40 mg; therefore, two 20 mg capsules of omeprazole and sodium bicarbonate should not be substituted for one capsule of omeprazole and sodium bicarbonate 40 mg.

Omeprazole and sodium bicarbonate capsules should be taken on an empty stomach at least one hour before a meal.

Table 1: Recommended Doses of Omeprazole and Sodium Bicarbonate by Indication for Adults 18 Years and Older
Indication | Recommended Dose | Frequency
Short-Term Treatment of Active Duodenal Ulcer | 20 mg | Once daily for 4 weeks [Most patients heal within 4 weeks. Some patients may require an additional 4 weeks of therapy. [See Clinical Studies (14.1).]] , [For additional information, [See Indications and Usage (1)]]
Benign Gastric Ulcer | 40 mg | Once daily for 4-8 weeks, [Controlled studies do not extend beyond 12 months. [See Clinical Studies (14).]]
Gastroesophageal Reflux Disease (GERD)
Symptomatic GERD (with no esophageal erosions) | 20 mg | Once daily for up to 4 weeks
Erosive Esophagitis | 20 mg | Once daily for 4-8 weeks
Maintenance of Healing of Erosive Esophagitis | 20 mg | Once daily

Special Populations

Hepatic Insufficiency

Consider dose reduction, particularly for maintenance of healing of erosive esophagitis. [See Clinical Pharmacology (12.3).]

Administration of Capsules

Omeprazole and sodium bicarbonate capsules should be swallowed intact with water. DO NOT USE OTHER LIQUIDS. DO NOT OPEN CAPSULE AND SPRINKLE CONTENTS INTO FOOD.

3 DOSAGE FORMS AND STRENGTHS

Omeprazole and Sodium Bicarbonate Capsules, 20mg/1100 mg: White to off white powder filled in size "00" hard gelatin capsules with opaque white colored cap and opaque white colored body imprinted "SG" on cap and "363" on body with black ink.

Omeprazole and Sodium Bicarbonate Capsules, 40 mg/1100 mg: White to off white powder filled in size "00" hard gelatin capsules with opaque light blue colored cap and opaque white colored body imprinted "SG" on cap and "364" on body with black ink.

4 CONTRAINDICATIONS

Omeprazole and sodium bicarbonate is contraindicated in patients with known hypersensitivity to any components of the formulation. Hypersensitivity reactions may include anaphylaxis, anaphylactic shock, angioedema, bronchospasm, acute interstitial nephritis, and urticaria. [See Adverse Reactions (6).]

5 WARNINGS AND PRECAUTIONS

5.1 Presence of Gastric Malignancy

In adults, symptomatic response to therapy with omeprazole does not preclude the presence of gastric malignancy. Consider additional follow-up and diagnostic testing in adult patients who have a suboptimal response or an early symptomatic relapse after completing treatment with a proton pump inhibitor PPI. In older patients, also consider an endoscopy.

5.2 Acute Interstitial Nephritis

Acute interstitial nephritis has been observed in patients taking PPIs including omeprazole and sodium bicarbonate. Acute interstitial nephritis may occur at any point during PPI therapy and is generally attributed to an idiopathic hypersensitivity reaction. Discontinue omeprazole and sodium bicarbonate if acute interstitial nephritis develops. [See Contraindications (4).]

5.3 Buffer Content

Each omeprazole and sodium bicarbonate capsule contains 1100 mg (13 mEq) of sodium bicarbonate. The total content of sodium in each capsule is 304 mg.

The sodium content of omeprazole and sodium bicarbonate products should be taken into consideration when administering to patients on a sodium restricted diet.

Because omeprazole and sodium bicarbonate products contain sodium bicarbonate, they should be used with caution in patients with Bartter's syndrome, hypokalemia, hypocalcemia, and problems with acid-base balance. Long-term administration of bicarbonate with calcium or milk can cause milk-alkali syndrome.

Chronic use of sodium bicarbonate may lead to systemic alkalosis and increased sodium intake can produce edema and weight increase.

5.4 Clostridium difficile-Associated Diarrhea

Published observational studies suggest that PPI therapy like omeprazole and sodium bicarbonate may be associated with an increased risk of Clostridium difficile-associated diarrhea, especially in hospitalized patients. This diagnosis should be considered for diarrhea that does not improve. [See Adverse Reactions (6.2).]

Patients should use the lowest dose and shortest duration of PPI therapy appropriate to the condition being treated.

5.5 Bone Fracture

Several published observational studies suggest that proton pump inhibitor (PPI) therapy may be associated with an increased risk for osteoporosis-related fractures of the hip, wrist, or spine. The risk of fracture was increased in patients who received high-dose, defined as multiple daily doses, and long-term PPI therapy (a year or longer). Patients should use the lowest dose and shortest duration of PPI therapy appropriate to the condition being treated. Patients at risk for osteoporosis-related fractures should be managed according to the established treatment guidelines. [See Dosage and Administration (2) and Adverse Reactions (6.2).]

5.6 Cutaneous and Systemic Lupus Erythematosus

Cutaneous lupus erythematosus (CLE) and systemic lupus erythematosus (SLE) have been reported in patients taking PPIs, including omeprazole. These events have occurred as both new onset and an exacerbation of existing autoimmune disease. The majority of PPI-induced lupus erythematous cases were CLE.

The most common form of CLE reported in patients treated with PPIs was subacute CLE (SCLE) and occurred within weeks to years after continuous drug therapy in patients ranging from infants to the elderly. Generally, histological findings were observed without organ involvement.

Systemic lupus erythematosus (SLE) is less commonly reported than CLE in patients receiving PPIs. PPI associated SLE is usually milder than non-drug induced SLE. Onset of SLE typically occurred within days to years after initiating treatment in patients ranging from young adults to the elderly. The majority of patients presented with rash; however, arthralgia and cytopenia were also reported.

Avoid administration of PPIs for longer than medically indicated. If signs or symptoms consistent with CLE or SLE are noted in patients receiving omeprazole and sodium bicarbonate, discontinue the drug and refer the patient to the appropriate specialist for evaluation. Most patients improve with discontinuation of the PPI alone in 4 to 12 weeks. Serological testing (e.g. ANA) may be positive and elevated serological test results may take longer to resolve than clinical manifestations.

5.7 Interaction with Clopidogrel

Avoid concomitant use of omeprazole and sodium bicarbonate with clopidogrel. Clopidogrel is a prodrug. Inhibition of platelet aggregation by clopidogrel is entirely due to an active metabolite. The metabolism of clopidogrel to its active metabolite can be impaired by use with concomitant medications, such as omeprazole, that interfere with CYP2C19 activity. Concomitant use of clopidogrel with 80 mg omeprazole reduces the pharmacological activity of clopidogrel, even when administered 12 hours apart. When using omeprazole and sodium bicarbonate, consider alternative antiplatelet therapy. [see Drug Interactions (7.5) and Clinical Pharmacology (12.3)]

5.8 Cyanocobalamin (Vitamin B-12) Deficiency

Daily treatment with any acid-suppressing medications over a long period of time (e.g., longer than 3 years) may lead to malabsorption of cyanocobalamin (vitamin B-12) caused by hypo- or achlorhydria. Rare reports of cyanocobalamin deficiency occurring with acid-suppressing therapy have been reported in the literature. This diagnosis should be considered if clinical symptoms consistent with cyanocobalamin deficiency are observed.

5.9 Hypomagnesemia

Hypomagnesemia, symptomatic and asymptomatic, has been reported rarely in patients treated with PPIs for at least three months, in most cases after a year of therapy. Serious adverse events include tetany, arrhythmias, and seizures. In most patients, treatment of hypomagnesemia required magnesium replacement and discontinuation of the PPI.

For patients expected to be on prolonged treatment or who take PPIs with medications such as digoxin or drugs that may cause hypomagnesemia (e.g., diuretics), health care professionals may consider monitoring magnesium levels prior to initiation of PPI treatment and periodically. [See Adverse Reactions (6.2).]

5.10 Concomitant Use of Omeprazole and Sodium Bicarbonate with St. John's Wort or Rifampin

Drugs which induce CYP2C19 or CYP34A (such as St. John's Wort or rifampin) can substantially decrease omeprazole concentrations [see Drug Interactions (7.2)]. Avoid concomitant use of omeprazole and sodium bicarbonate with St John's Wort or rifampin.

5.11 Interactions with Investigations for Neuroendocrine Tumors

Serum chromogranin A (CgA) levels increase secondary to drug-induced decreases in gastric acidity. The increased CgA level may cause false positive results in diagnostic investigations for neuroendocrine tumors. Providers should temporarily stop omeprazole treatment before assessing CgA levels and consider repeating the test if initial CgA levels are high. If serial tests are performed (e.g., for monitoring), the same commercial laboratory should be used for testing, as reference ranges between tests may vary. [See Pharmacodynamics (12.2).]

5.12 Concomitant Use of Omeprazole and Sodium Bicarbonate with Methotrexate

Literature suggests that concomitant use of PPIs with methotrexate (primarily at high dose; see methotrexate prescribing information) may elevate and prolong serum levels of methotrexate and/or its metabolite, possibly leading to methotrexate toxicities. In high-dose methotrexate administration, a temporary withdrawal of the PPI may be considered in some patients. [See Drug Interactions (7.8).]

5.13 Fundic Gland Polyps

PPI use is associated with an increased risk of fundic gland polyps that increases with long-term use, especially beyond one year. Most PPIs users who developed fundic gland polyps were asymptomatic and fundic gland polyps were identified incidentally on endoscopy. Use the shortest duration of PPI therapy appropriate to the condition being treated.

6 ADVERSE REACTIONS

The following serious adverse reactions are described below and elsewhere in labeling:

- Acute Interstitial Nephritis [see Warnings and Precautions (5.2)]
- Clostridium difficile-Associated Diarrhea [see Warnings and Precautions (5.4)]
- Bone Fracture [see Warnings and Precautions (5.5)]
- Cutaneous and Systemic Lupus Erythematosus [see Warnings and Precautions (5.6)]
- Cyanocobalamin (Vitamin B-12) Deficiency [see Warnings and Precautions (5.8)]
- Hypomagnesemia [see Warnings and Precautions (5.9)]
- Fundic Gland Polyps [see Warnings and Precautions (5.13)]

6.1 Clinical Trials Experience

Because clinical trials are conducted under widely varying conditions, adverse reaction rates observed in the clinical trials of a drug cannot be directly compared to rates in the clinical trials of another drug and may not reflect the rates observed in clinical practice.

In the U.S. clinical trial population of 465 patients, the adverse reactions summarized in Table 2 were reported to occur in 1% or more of patients on therapy with omeprazole. Numbers in parentheses indicate percentages of the adverse reactions considered by investigators as possibly, probably or definitely related to the drug.

Table 2: Adverse Reactions Occurring in 1% or More of Patients on Omeprazole Therapy
 | Omeprazole (n = 465) | Placebo (n = 64) | Ranitidine (n = 195)
Headache | 6.9 (2.4) | 6.3 | 7.7 (2.6)
Diarrhea | 3.0 (1.9) | 3.1 (1.6) | 2.1 (0.5)
Abdominal Pain | 2.4 (0.4) | 3.1 | 2.1
Nausea | 2.2 (0.9) | 3.1 | 4.1 (0.5)
URI | 1.9 | 1.6 | 2.6
Dizziness | 1.5 (0.6) | 0.0 | 2.6 (1.0)
Vomiting | 1.5 (0.4) | 4.7 | 1.5 (0.5)
Rash | 1.5 (1.1) | 0.0 | 0.0
Constipation | 1.1 (0.9) | 0.0 | 0.0
Cough | 1.1 | 0.0 | 1.5
Asthenia | 1.1 (0.2) | 1.6 (1.6) | 1.5 (1.0)
Back Pain | 1.1 | 0.0 | 0.5

Table 3 summarizes the adverse reactions that occurred in 1% or more of omeprazole-treated patients from international double-blind and open-label clinical trials in which 2,631 patients and subjects received omeprazole.

Table 3: Incidence of Adverse Reactions ≥ 1% Causal Relationship not Assessed
 | Omeprazole (n = 2631) | Placebo (n = 120)
Body as a Whole, Site Unspecified
Abdominal Pain | 5.2 | 3.3
Asthenia | 1.3 | 0.8
Digestive System
Constipation | 1.5 | 0.8
Diarrhea | 3.7 | 2.5
Flatulence | 2.7 | 5 .8
Nausea | 4.0 | 6.7
Vomiting | 3.2 | 10.0
Acid Regurgitation | 1.9 | 3.3
Nervous System/Psychiatric
Headache | 2.9 | 2.5

6.2 Postmarketing Experience

The following adverse reactions have been identified during post-approval use of omeprazole. Because these reactions are reported voluntarily from a population of uncertain size, it is not always possible to reliably estimate their frequency or establish a causal relationship to drug exposure.

Body as a Whole: Hypersensitivity reactions, including anaphylaxis, anaphylactic shock, angioedema, bronchospasm, interstitial nephritis, urticaria (see also Error! Hyperlink reference not valid. below), fever, pain, fatigue, malaise, and systemic lupus erythematosus.

Cardiovascular: Chest pain or angina, tachycardia, bradycardia, palpitation, elevated blood pressure, and peripheral edema.

Gastrointestinal: Pancreatitis (some fatal), anorexia, irritable colon, flatulence, fecal discoloration, esophageal candidiasis, mucosal atrophy of the tongue, dry mouth, stomatitis, abdominal swelling and fundic gland polyps. Gastroduodenal carcinoids have been reported in patients with Zollinger-Ellison syndrome on long-term treatment with omeprazole. This finding is believed to be a manifestation of the underlying condition, which is known to be associated with such tumors.

Hepatic: Mild and, rarely, marked elevations of liver function tests [ALT (SGPT), AST (SGOT), γ-glutamyltranspeptidase, alkaline phosphatase, and bilirubin (jaundice)]. In rare instances, overt liver disease has occurred, including hepatocellular, cholestatic, or mixed hepatitis, liver necrosis (some fatal), hepatic failure (some fatal), and hepatic encephalopathy.

Infections and Infestations: Clostridium difficile- associated diarrhea.

Metabolism and Nutritional Disorders: Hyponatremia, hypoglycemia, hypomagnesemia, and weight gain.

Musculoskeletal: Muscle cramps, myalgia, muscle weakness, joint pain, bone fracture, and leg pain.

Nervous System/Psychiatric: Psychic disturbances including depression, agitation, aggression, hallucinations, confusion, insomnia, nervousness, tremors, apathy, somnolence, anxiety, dream abnormalities; vertigo; paresthesia; and hemifacial dysesthesia.

Respiratory: Epistaxis, pharyngeal pain.

Skin: Severe generalized skin reactions including toxic epidermal necrolysis (TEN; some fatal), Stevens-Johnson syndrome, cutaneous lupus erythematosus and erythema multiforme (some severe); purpura and/or petechiae (some with rechallenge); skin inflammation, urticaria, angioedema, pruritus, photosensitivity, alopecia, dry skin, and hyperhidrosis.

Special Senses: Tinnitus, taste perversion.

Ocular: Blurred vision, ocular irritation, dry eye syndrome, optic atrophy, anterior ischemic optic neuropathy, optic neuritis and double vision.

Urogenital: Interstitial nephritis (some with positive rechallenge), urinary tract infection, microscopic pyuria, urinary frequency, elevated serum creatinine, proteinuria, hematuria, glycosuria, testicular pain, and gynecomastia.

Hematologic: Rare instances of pancytopenia, agranulocytosis (some fatal), thrombocytopenia, neutropenia, leukopenia, anemia, leukocytosis, and hemolytic anemia have been reported.

The incidence of clinical adverse experiences in patients greater than 65 years of age was similar to that in patients 65 years of age or less.

Additional adverse reactions that could be caused by sodium bicarbonate include metabolic alkalosis, seizures, and tetany.

7 DRUG INTERACTIONS

7.1 Drugs for Which Gastric pH Can Affect Bioavailability

Due to its effects on gastric acid secretion, omeprazole can reduce the absorption of drugs where gastric pH is an important determinant of their bioavailability. Like with other drugs that decrease the intragastric acidity, the absorption of drugs such as ketoconazole, atazanavir, iron salts, erlotinib, and mycophenolate mofetil (MMF) can decrease, while the absorption of drugs such as digoxin can increase during treatment with omeprazole.

Concomitant treatment with omeprazole (20 mg daily) and digoxin in healthy subjects increased the bioavailability of digoxin by 10% (30% in two subjects). Coadministration of digoxin with omeprazole and sodium bicarbonate is expected to increase the systemic exposure of digoxin. Therefore, patients may need to be monitored when digoxin is taken concomitantly with omeprazole and sodium bicarbonate.

Co-administration of omeprazole in healthy subjects and in transplant patients receiving MMF has been reported to reduce the exposure to the active metabolite, mycophenolic acid (MPA), possibly due to a decrease in MMF solubility at an increased gastric pH. The clinical relevance of reduced MPA exposure on organ rejection has not been established in transplant patients receiving omeprazole and sodium bicarbonate and MMF. Use omeprazole with caution in transplant patients receiving MMF. [See Clinical Pharmacology (12.3).]

7.2 Drugs Metabolized by Cytochrome P450 (CYP)

Omeprazole can prolong the elimination of diazepam, warfarin and phenytoin, drugs that are metabolized by oxidation in the liver. There have been reports of increased international normalized ratio (INR) and prothrombin time in patients receiving proton pump inhibitors, including omeprazole, and warfarin concomitantly. Increases in INR and prothrombin time may lead to abnormal bleeding and even death. Patients treated with proton pump inhibitors and warfarin may need to be monitored for increases in INR and prothrombin time.

Although in normal subjects no interaction with theophylline or propranolol was found, there have been clinical reports of interaction with other drugs metabolized via the cytochrome P450 system (e.g., cyclosporine, disulfiram, benzodiazepines). Patients should be monitored to determine if it is necessary to adjust the dosage of these drugs when taken concomitantly with omeprazole and sodium bicarbonate.

Concomitant administration of omeprazole and voriconazole (a combined inhibitor of CYP2C19 and CYP3A4) resulted in more than doubling of the omeprazole exposure. Dose adjustment of omeprazole is not normally required. When voriconazole (400 mg every 12 hours for one day, then 200 mg for 6 days) was given with omeprazole (40 mg once daily for 7 days) to healthy subjects, it significantly increased the steady-state Cmax and AUC0-24 of omeprazole, an average of 2 times (90% CI: 1.8, 2.6) and 4 times (90% CI: 3.3, 4.4) respectively as compared to when omeprazole was given without voriconazole.

Drugs known to induce CYP2C19 or CYP3A4 (such as rifampin) may lead to decreased omeprazole serum levels. In a crossover study in 12 healthy male subjects, St. John's wort (300 mg three times daily for 14 days), an inducer of CYP3A4, decreased the systemic exposure of omeprazole in CYP2C19 poor metabolizers (Cmax and AUC decreased by 37.5% and 37.9%, respectively) and extensive metabolizers (Cmax and AUC decreased by 49.6% and 43.9%, respectively). Avoid concomitant use of St. John's Wort or rifampin with omeprazole.

7.3 Antiretroviral Agents

Concomitant administration of atazanavir and proton pump inhibitors is not recommended. Co-administration of atazanavir with proton pump inhibitors is expected to substantially decrease atazanavir plasma concentrations and thereby reduce its therapeutic effect.

Omeprazole has been reported to interact with some antiretroviral drugs. The clinical importance and the mechanisms behind these interactions are not always known. Increased gastric pH during omeprazole treatment may change the absorption of the antiretroviral drug. Other possible interaction mechanisms are via CYP2C19. For some antiretroviral drugs, such as atazanavir and nelfinavir, decreased serum levels have been reported when given together with omeprazole. Following multiple doses of nelfinavir (1250 mg, twice daily) and omeprazole (40 mg, daily), AUC was decreased by 36% and 92%, Cmax by 37% and 89% and Cmin by 39% and 75% respectively for nelfinavir and M8. Following multiple doses of atazanavir (400 mg, daily) and omeprazole (40 mg, daily, 2 hours before atazanavir), AUC was decreased by 94%, Cmax by 96%, and Cmin by 95%. Concomitant administration with omeprazole and drugs such as atazanavir and nelfinavir is therefore not recommended.

Increased Concentration of Saquinavir

For other antiretroviral drugs, such as saquinavir, elevated serum levels have been reported with an increase in AUC by 82%, in Cmax by 75% and in Cmin by 106% following multiple dosing of saquinavir/ritonavir (1000/100 mg) twice daily for 15 days with omeprazole 40 mg daily co-administered days 11 to 15. Dose reduction of saquinavir should be considered from the safety perspective for individual patients. There are also some antiretroviral drugs of which unchanged serum levels have been reported when given with omeprazole.

7.4 Combination Therapy with Clarithromycin

Concomitant administration of clarithromycin with other drugs can lead to serious adverse reactions due to drug interaction [See Warnings and Precautions in prescribing information for clarithromycin]. Because of these drug interactions, clarithromycin is contraindicated for co-administration with certain drugs [See Contraindications in prescribing information for clarithromycin.]

7.5 Clopidogrel

Omeprazole is an inhibitor of CYP2C19 enzyme. Clopidogrel is metabolized to its active metabolite in part by CYP2C19. Concomitant use of omeprazole 80 mg results in reduced plasma concentrations of the active metabolite of clopidogrel and a reduction in platelet inhibition. Avoid concomitant administration of omeprazole and sodium bicarbonate with clopidogrel. When using omeprazole and sodium bicarbonate, consider use of alternative anti-platelet therapy. [See Clinical Pharmacology (12.3.)]

7.6 Tacrolimus

Concomitant administration of omeprazole and tacrolimus may increase the serum levels of tacrolimus.

7.7 Interactions with Investigations of Neuroendocrine Tumors

Drug-induced decrease in gastric acidity results in enterochromaffin-like cell hyperplasia and increased Chromogranin A levels which may interfere with investigations for neuroendocrine tumors. [See Clinical Pharmacology (12).]

7.8 Methotrexate

Case reports, published population pharmacokinetic studies, and retrospective analyses suggest that concomitant administration of PPIs and methotrexate (primarily at high dose; see methotrexate prescribing information) may elevate and prolong serum levels of methotrexate and/or its metabolite hydroxymethotrexate. However, no formal drug interaction studies of methotrexate with PPIs have been conducted. [See Warnings and Precautions (5.12).]

8 USE IN SPECIFIC POPULATIONS

8.1 Pregnancy

TERATOGENIC EFFECTS

Pregnancy Category C

Risk Summary

There are no adequate and well-controlled studies on the use of omeprazole and sodium bicarbonate in pregnant women. Available epidemiologic data fail to demonstrate an increased risk of major congenital malformations or other adverse pregnancy outcomes with first trimester omeprazole use. Teratogenicity was not observed in animal reproduction studies with administration of oral esomeprazole magnesium in rats and rabbits with doses about 68 times and 42 times, respectively, an oral human dose of 40 mg (based on body surface area basis for a 60 kg person). However, changes in bone morphology were observed in offspring of rats dosed through most of pregnancy and lactation at doses equal to or greater than approximately 33.6 times an oral human dose of 40 mg (see Error! Hyperlink reference not valid.). Because of the observed effect at high doses of esomeprazole magnesium on developing bone in rat studies, omeprazole and sodium bicarbonate should be used during pregnancy only if the potential benefit justifies the potential risk to the fetus.

Human Data

Four published epidemiological studies compared the frequency of congenital abnormalities among infants born to women who used omeprazole during pregnancy with the frequency of abnormalities among infants of women exposed to H2-receptor antagonists or other controls.

A population-based retrospective cohort epidemiological study from the Swedish Medical Birth Registry, covering approximately 99% of pregnancies, from 1995-99, reported on 955 infants (824 exposed during the first trimester with 39 of these exposed beyond first trimester, and 131 exposed after the first trimester) whose mothers used omeprazole during pregnancy. The number of infants exposed in utero to omeprazole that had any malformation, low birth weight, low Apgar score, or hospitalization was similar to the number observed in this population. The number of infants born with ventricular septal defects and the number of stillborn infants was slightly higher in the omeprazole-exposed infants than the expected number in this population.

A population-based retrospective cohort study covering all live births in Denmark from 1996-2009, reported on 1,800 live births whose mothers used omeprazole during the first trimester of pregnancy and 837,317 live births whose mothers did not use any proton pump inhibitor. The overall rate of birth defects in infants born to mothers with first trimester exposure to omeprazole was 2.9% and 2.6% in infants born to mothers not exposed to any proton pump inhibitor during the first trimester.

A retrospective cohort study reported on 689 pregnant women exposed to either H2-blockers or omeprazole in the first trimester (134 exposed to omeprazole) and 1,572 pregnant women unexposed to either during the first trimester. The overall malformation rate in offspring born to mothers with first trimester exposure to omeprazole, an H2-blocker, or were unexposed was 3.6%, 5.5%, and 4.1% respectively.

A small prospective observational cohort study followed 113 women exposed to omeprazole during pregnancy (89% first trimester exposures). The reported rate of major congenital malformations was 4% in the omeprazole group, 2% in controls exposed to non-teratogens, and 2.8% in disease-paired controls. Rates of spontaneous and elective abortions, preterm deliveries, gestational age at delivery, and mean birth weight were similar among the groups.

Several studies have reported no apparent adverse short-term effects on the infant when single-dose oral or intravenous omeprazole was administered to over 200 pregnant women as premedication for cesarean section under general anesthesia.

Animal Data

Reproductive studies conducted with omeprazole in rats at oral doses up to 138 mg/kg/day (about 33.6 times an oral human dose of 40 mg on a body surface area basis) and in rabbits at doses up to 69 mg/kg/day (about 33.6 times an oral human dose of 40 mg on a body surface area basis) did not disclose any evidence for a teratogenic potential of omeprazole. In rabbits, omeprazole in a dose range of 6.9 to 69.1 mg/kg/day (about 3.36 to 33.6 times an oral human dose of 40 mg on a body surface area basis) produced dose-related increases in embryo-lethality, fetal resorptions, and pregnancy disruptions. In rats, dose-related embryo/fetal toxicity and postnatal developmental toxicity were observed in offspring resulting from parents treated with omeprazole at 13.8 to 138.0 mg/kg/day (about 3.36 to 33.6 times an oral human dose of 40 mg on a body surface area basis).

Reproduction studies have been performed with esomeprazole magnesium in rats at oral doses up to 280 mg/kg/day (about 68 times an oral human dose of 40 mg on a body surface area basis) and in rabbits at oral doses up to 86 mg/kg/day (about 42 times an oral human dose of 40 mg on a body surface area basis) and have revealed no evidence of impaired fertility or harm to the fetus due to esomeprazole magnesium.

A pre- and postnatal developmental toxicity study in rats with additional endpoints to evaluate bone development were performed with the S-enantiomer, esomeprazole magnesium at oral doses of 14 to 280 mg/kg/day (about 3.4 to 68 times an oral human dose of 40 mg of esomeprazole on a body surface area basis). Neonatal/early postnatal (birth to weaning) survival was decreased at doses equal to or greater than 138 mg/kg/day (about 33.6 times an oral human dose of 40 mg on a body surface area basis). Body weight and body weight gain were reduced and neurobehavioral or general developmental delays in the immediate post-weaning timeframe were evident at doses equal to or greater than 69 mg /kg/day (about 16.8 times an oral human dose of 40 mg on a body surface area basis). In addition, decreased femur length, width and thickness of cortical bone, decreased thickness of the tibial growth plate and minimal to mild bone marrow hypocellularity were noted at doses of esomeprazole magnesium equal to or greater than 14 mg/kg/day (about 3.4 times an oral human dose of 40 mg on a body surface area basis). Physeal dysplasia in the femur was observed in offspring of rats treated with oral doses of esomeprazole magnesium at doses equal to or greater than 138 mg/kg/day (about 33.6 times an oral human dose of 40 mg on a body surface area basis).

Effects on maternal bone were observed in pregnant and lactating rats in a pre- and postnatal toxicity study when esomeprazole magnesium was administered at oral doses of 14 to 280 mg/kg/day (about 3.4 to 68 times an oral human dose of 40 mg on a body surface area basis). When rats were dosed from gestational day 7 through weaning on postnatal day 21, a statistically significant decrease in maternal femur weight of up to 14% (as compared to placebo treatment) was observed at doses of esomeprazole magnesium equal to or greater than 138 mg/kg/day (about 33.6 times an oral human dose of 40 mg on a body surface area basis).

A pre- and post natal development study in rats with esomeprazole strontium (using equimolar doses compared to esomeprazole magnesium study) produced similar results in dams and pups as described above.

8.3 Nursing Mothers

Omeprazole concentrations have been measured in breast milk of a woman following oral administration of 20 mg. The peak concentration of omeprazole in breast milk was less than 7% of the peak serum concentration. The concentration will correspond to 0.004 mg of omeprazole in 200 mL of milk. Because omeprazole is excreted in human milk, because of the potential for serious adverse reactions in nursing infants from omeprazole, and because of the potential for tumorigenicity shown for omeprazole in rat carcinogenicity studies, a decision should be made to discontinue nursing or to discontinue the drug, taking into account the importance of the drug to the mother. In addition, sodium bicarbonate should be used with caution in nursing mothers.

8.4 Pediatric Use

Safety and effectiveness of omeprazole and sodium bicarbonate have not been established in pediatric patients less than 18 years of age.

Juvenile Animal Data

In a juvenile rat toxicity study, esomeprazole was administered with both magnesium and strontium salts at oral doses about 34 to 68 times a daily human dose of 40 mg on a body surface area basis. Increases in death were seen at the high dose, and at all doses of esomeprazole, there were decreases in body weight, body weight gain, femur weight and femur length, and decreases in overall growth. [See Nonclinical Toxicology (13.2).]

8.5 Geriatric Use

Omeprazole was administered to over 2000 elderly individuals (≥ 65 years of age) in clinical trials in the U.S. and Europe. There were no differences in safety and effectiveness between the elderly and younger subjects. Other reported clinical experience has not identified differences in response between the elderly and younger subjects, but greater sensitivity of some older individuals cannot be ruled out.

Pharmacokinetic studies with buffered omeprazole have shown the elimination rate was somewhat decreased in the elderly and bioavailability was increased. The plasma clearance of omeprazole was 250 mL/min (about half that of young subjects). The plasma half-life averaged one hour, about twice that in nonelderly, healthy subjects taking omeprazole and sodium bicarbonate. However, no dosage adjustment is necessary in the elderly. [See Clinical Pharmacology (12.3).]

8.6 Hepatic Impairment

Consider dose reduction, particularly for maintenance of healing of erosive esophagitis. [See Clinical Pharmacology (12.3).]

8.7 Renal Impairment

No dose reduction is necessary. [See Clinical Pharmacology (12.3).]

8.8 Asian Population

Recommend dose reduction, particularly for maintenance of healing of erosive esophagitis. [See Clinical Pharmacology (12.3).]

10 OVERDOSAGE

Reports have been received of overdosage with omeprazole in humans. Doses ranged up to 2400 mg (120 times the usual recommended clinical dose). Manifestations were variable, but included confusion, drowsiness, blurred vision, tachycardia, nausea, vomiting, diaphoresis, flushing, headache, dry mouth, and other adverse reactions similar to those seen in normal clinical experience [See Adverse Reactions (6)]. Symptoms were transient, and no serious clinical outcome has been reported when omeprazole was taken alone. No specific antidote for omeprazole overdosage is known. Omeprazole is extensively protein bound and is, therefore, not readily dialyzable. In the event of overdosage, treatment should be symptomatic and supportive.

As with the management of any overdose, the possibility of multiple drug ingestion should be considered. For current information on treatment of any drug overdose, a certified Regional Poison Control Center should be contacted. Telephone numbers are listed in the Physicians' Desk Reference (PDR) or local telephone book.

Single oral doses of omeprazole at 1350, 1339, and 1200 mg/kg were lethal to mice, rats, and dogs, respectively. Animals given these doses showed sedation, ptosis, tremors, convulsions, and decreased activity, body temperature, and respiratory rate and increased depth of respiration.

In addition, a sodium bicarbonate overdose may cause hypocalcemia, hypokalemia, hypernatremia, and seizures.

11 DESCRIPTION

Omeprazole and sodium bicarbonate is a combination of omeprazole, a proton-pump inhibitor, and sodium bicarbonate, an antacid. Omeprazole is a substituted benzimidazole, 5-methoxy-2-[[(4-methoxy-3,5dimethyl-2-pyridinyl)methyl]sulfinyl]-1H-benzimidazole, a racemic mixture of two enantiomers that inhibits gastric acid secretion. Its empirical formula is C17H19N3O3S, with a molecular weight of 345.42. The structural formula is:

Omeprazole, USP is a white or almost white powder which melts with decomposition at about 155°C. Soluble in dichloromethane, practically insoluble in water. The stability of omeprazole is a function of pH; it is rapidly degraded in acid media, but has acceptable stability under alkaline conditions.

Omeprazole and sodium bicarbonate is supplied as immediate-release capsules. Each capsule contains either 40 mg or 20 mg of omeprazole and 1100 mg of sodium bicarbonate with the following excipients: croscarmellose sodium and sodium stearyl fumarate. The capsules consist of gelatin and titanium dioxide. In addition the 20 mg/1100 mg capsule shell contains sodium lauryl sulfate and the 40 mg/1100 mg capsule shell contains FD&C Blue 1. The capsules are printed with edible ink containing black iron oxide, butyl alcohol, dehydrated alcohol, isopropyl alcohol, propylene glycol, potassium hydroxide, shellac and strong ammonia solution.

12 CLINICAL PHARMACOLOGY

12.1 Mechanism of Action

Omeprazole belongs to a class of antisecretory compounds, the substituted benzimidazoles, that do not exhibit anticholinergic or H2 histamine antagonistic properties, but that suppress gastric acid secretion by specific inhibition of the H+/K+ ATPase enzyme system at the secretory surface of the gastric parietal cell. Because this enzyme system is regarded as the acid (proton) pump within the gastric mucosa, omeprazole has been characterized as a gastric acid-pump inhibitor, in that it blocks the final step of acid production. This effect is dose related and leads to inhibition of both basal and stimulated acid secretion irrespective of the stimulus. Animal studies indicate that after rapid disappearance from plasma, omeprazole can be found within the gastric mucosa for a day or more.

Omeprazole is acid labile and thus rapidly degraded by gastric acid. Omeprazole and sodium bicarbonate capsules are immediate-release formulations that contain sodium bicarbonate which raises the gastric pH and thus protects omeprazole from acid degradation.

12.2 Pharmacodynamics

Antisecretory Activity

Results from a PK/PD study of the antisecretory effect of repeated once-daily dosing of 40 mg and 20 mg of omeprazole and sodium bicarbonate oral suspension in healthy subjects are shown in Table 5 below.

Table 4: Effect of Omeprazole and Sodium Bicarbonate Oral Suspension on Intragastric pH, Day 7
Parameter | Omeprazole/Sodium Bicarbonate
Parameter | 40 mg/1680 mg (n = 24) | 20 mg/1680 mg (n = 28)
% Decrease from Baseline for Integrated Gastric Acidity (mmol∙hr/L) | 84% | 82%
Coefficient of variation | 20% | 24%
% Time Gastric pH > 4 [p < 0.05 20 mg vs. 40 mg] (Hours) | 77 (18.6 h) | 51 (12.2 h)
Coefficient of variation | 27% | 43%
Median pH | 5.2 | 4.2
Coefficient of variation | 17% | 37%
Note: Values represent medians. All parameters were measured over a 24-hour period.

Results from a separate PK/PD study of antisecretory effect on repeated once daily dosing of 40 mg/1100 mg and 20 mg/1100 mg of omeprazole and sodium bicarbonate capsules in healthy subjects show similar effects in general on the above three PD parameters as those for omeprazole and sodium bicarbonate 40 mg/1680 mg and 20 mg/1680 mg oral suspension, respectively.

The antisecretory effect lasts longer than would be expected from the very short (1 hour) plasma half-life, apparently due to irreversible binding to the parietal H+/K+ ATPase enzyme.

Enterochromaffin-like (ECL) Cell Effects

In 24-month carcinogenicity studies in rats, a dose-related significant increase in gastric carcinoid tumors and ECL cell hyperplasia was observed in both male and female animals [see Nonclinical Toxicology (13.1)]. Carcinoid tumors have also been observed in rats subjected to fundectomy or long-term treatment with other proton pump inhibitors or high doses of H2-receptor antagonists. Human gastric biopsy specimens have been obtained from more than 3000 patients treated with omeprazole in long-term clinical trials. The incidence of ECL cell hyperplasia in these studies increased with time; however, no case of ECL cell carcinoids, dysplasia, or neoplasia has been found in these patients. These studies are of insufficient duration and size to rule out the possible influence of long-term administration of omeprazole on the development of any premalignant or malignant conditions.

Serum Gastrin Effects

In studies involving more than 200 patients, serum gastrin levels increased during the first 1 to 2 weeks of once-daily administration of therapeutic doses of omeprazole in parallel with inhibition of acid secretion. No further increase in serum gastrin occurred with continued treatment. In comparison with histamine H2-receptor antagonists, the median increases produced by 20 mg doses of omeprazole were higher (1.3 to 3.6 fold vs. 1.1 to 1.8 fold increase). Gastrin values returned to pretreatment levels, usually within 1 to 2 weeks after discontinuation of therapy.

Increased gastrin causes enterochromaffin-like cell hyperplasia and increased serum Chromogranin A (CgA) levels. The increased CgA levels may cause false positive results in diagnostic investigations for neuroendocrine tumors.

Other Effects

Systemic effects of omeprazole in the CNS, cardiovascular and respiratory systems have not been found to date. Omeprazole, given in oral doses of 30 or 40 mg for 2 to 4 weeks, had no effect on thyroid function, carbohydrate metabolism, or circulating levels of parathyroid hormone, cortisol, estradiol, testosterone, prolactin, cholecystokinin or secretin.

No effect on gastric emptying of the solid and liquid components of a test meal was demonstrated after a single dose of omeprazole 90 mg. In healthy subjects, a single I.V. dose of omeprazole (0.35 mg/kg) had no effect on intrinsic factor secretion. No systematic dose-dependent effect has been observed on basal or stimulated pepsin output in humans. However, when intragastric pH is maintained at 4.0 or above, basal pepsin output is low, and pepsin activity is decreased.

As do other agents that elevate intragastric pH, omeprazole administered for 14 days in healthy subjects produced a significant increase in the intragastric concentrations of viable bacteria. The pattern of the bacterial species was unchanged from that commonly found in saliva. All changes resolved within three days of stopping treatment.

The course of Barrett's esophagus in 106 patients was evaluated in a U.S. double-blind controlled study of omeprazole 40 mg twice daily for 12 months followed by 20 mg twice daily for 12 months or ranitidine 300 mg twice daily for 24 months. No clinically significant impact on Barrett's mucosa by antisecretory therapy was observed. Although neosquamous epithelium developed during antisecretory therapy, complete elimination of Barrett's mucosa was not achieved. No significant difference was observed between treatment groups in development of dysplasia in Barrett's mucosa, and no patient developed esophageal carcinoma during treatment. No significant differences between treatment groups were observed in development of ECL cell hyperplasia, corpus atrophic gastritis, corpus intestinal metaplasia, or colon polyps exceeding 3 mm in diameter.

12.3 Pharmacokinetics

Absorption

In separate in vivo bioavailability studies, when omeprazole and sodium bicarbonate oral suspension and capsules are administered on an empty stomach 1 hour prior to a meal, the absorption of omeprazole is rapid, with mean peak plasma levels (% CV) of omeprazole being 1954 ng/mL (33%) and 1526 ng/mL (49%), respectively, and time to peak of approximately 30 minutes (range 10-90 min) after a single-dose or repeated-dose administration. Absolute bioavailability of omeprazole and sodium bicarbonate powder for oral suspension (compared to I.V. administration) is about 30-40% at doses of 20 to 40 mg, due in large part to presystemic metabolism.

When omeprazole and sodium bicarbonate oral suspension 40 mg/1680 mg was administered in a two-dose loading regimen, the omeprazole AUC(0-inf) (ng∙hr/mL) was 1665 after Dose 1 and 3356 after Dose 2, while Tmax was approximately 30 minutes for both Dose 1 and Dose 2.

Following single or repeated once daily dosing, peak plasma concentrations of omeprazole from omeprazole and sodium bicarbonate are approximately proportional from 20 to 40 mg doses, but a greater than linear mean AUC (three-fold increase) is observed when doubling the dose to 40 mg. The bioavailability of omeprazole from omeprazole and sodium bicarbonate increases upon repeated administration.

When omeprazole and sodium bicarbonate is administered 1 hour after a meal, the omeprazole AUC is reduced by approximately 24% relative to administration 1 hour prior to a meal.

Distribution

Omeprazole is bound to plasma proteins. Protein binding is approximately 95%.

Metabolism

Following single-dose oral administration of omeprazole, the majority of the dose (about 77%) is eliminated in urine as at least six metabolites. Two metabolites have been identified as hydroxyomeprazole and the corresponding carboxylic acid. The remainder of the dose was recoverable in feces. This implies a significant biliary excretion of the metabolites of omeprazole. Three metabolites have been identified in plasma – the sulfide and sulfone derivatives of omeprazole, and hydroxyomeprazole. These metabolites have very little or no antisecretory activity.

Excretion

Following single-dose oral administration of omeprazole, little, if any, unchanged drug is excreted in urine. The mean plasma omeprazole half-life in healthy subjects is approximately 1 hour (range 0.4 to 3.2 hours) and the total body clearance is 500-600 mL/min.

Concomitant Use with Clopidogrel

In a crossover clinical study, 72 healthy subjects were administered clopidogrel (300 mg loading dose followed by 75 mg per day) alone and with omeprazole (80 mg at the same time as clopidogrel) for 5 days. The exposure to the active metabolite of clopidogrel was decreased by 46% (Day 1) and 42% (Day 5) when clopidogrel and omeprazole were administered together.

Results from another crossover study in healthy subjects showed a similar pharmacokinetic interaction between clopidogrel (300 mg loading dose/75 mg daily maintenance dose) and omeprazole 80 mg daily when coadministered for 30 days. Exposure to the active metabolite of clopidogrel was reduced by 41% to 46% over this time period.

In another study, 72 healthy subjects were given the same doses of clopidogrel and 80 mg Omeprazole, but the drugs were administered 12 hours apart; the results were similar, indicating that administering clopidogrel and omeprazole at different times does not prevent their interaction.

Concomitant Use with Mycophenolate Mofetil

Administration of omeprazole 20 mg twice daily for 4 days and a single 1000 mg dose of MMF approximately one hour after the last dose of omeprazole to 12 healthy subjects in a crossover study resulted in a 52% reduction in the Cmax and 23% reduction in the AUC of MPA.

Special Populations

Geriatric

The elimination rate of omeprazole was somewhat decreased in the elderly, and bioavailability was increased. Omeprazole was 76% bioavailable when a single 40 mg oral dose of omeprazole (buffered solution) was administered to healthy elderly subjects versus 58% in young subjects given the same dose. Nearly 70% of the dose was recovered in urine as metabolites of omeprazole, and no unchanged drug was detected. The plasma clearance of omeprazole was 250 mL/min (about half that of young subjects), and its plasma half-life averaged one hour, similar to that of young healthy subjects.

Pediatric

The pharmacokinetics of omeprazole and sodium bicarbonate has not been studied in patients < 18 years of age.

Gender

There are no known differences in the absorption or excretion of omeprazole between males and females.

Hepatic Insufficiency

In patients with chronic hepatic disease, the bioavailability of omeprazole from a buffered solution increased to approximately 100% compared to an I.V. dose, reflecting decreased first-pass effect, and the mean plasma half-life of the drug increased to nearly 3 hours compared to the mean half-life of 1 hour in normal subjects. Plasma clearance averaged 70 mL/min, compared to a value of 500-600 mL/min in normal subjects. Dose reduction, particularly where maintenance of healing of erosive esophagitis is indicated, for the hepatically impaired should be considered.

Renal Insufficiency

In patients with chronic renal impairment, whose creatinine clearance ranged between 10 and 62 mL/min/1.73 m^2, the disposition of omeprazole from a buffered solution was very similar to that in healthy subjects, although there was a slight increase in bioavailability. Because urinary excretion is a primary route of excretion of omeprazole metabolites, their elimination slowed in proportion to the decreased creatinine clearance. No dose reduction is necessary in patients with renal impairment.

Asian Population

In pharmacokinetic studies of single 20 mg omeprazole doses, an increase in AUC of approximately four-fold was noted in Asian subjects compared to Caucasians. Dose adjustment, particularly where maintenance of healing of erosive esophagitis is indicated, for Asian subjects should be considered.

13 NONCLINICAL TOXICOLOGY

13.1 Carcinogenesis, Mutagenesis, Impairment of Fertility

In two 24-month carcinogenicity studies in rats, omeprazole at daily doses of 1.7, 3.4, 13.8, 44.0 and 140.8 mg/kg/day (approximately 0.4 to 34.2 times the human dose of 40 mg/day on a body surface area basis) produced gastric ECL cell carcinoids in a dose-related manner in both male and female rats; the incidence of this effect was markedly higher in female rats, which had higher blood levels of omeprazole. Gastric carcinoids seldom occur in the untreated rat. In addition, ECL cell hyperplasia was present in all treated groups of both sexes. In one of these studies, female rats were treated with 13.8 mg omeprazole/kg/day (approximately 3.36 times the human dose of 40 mg/day on a body surface area basis) for one year, then followed for an additional year without the drug. No carcinoids were seen in these rats. An increased incidence of treatment-related ECL cell hyperplasia was observed at the end of one year (94% treated versus 10% controls). By the second year the difference between treated and control rats was much smaller (46% versus 26%) but still showed more hyperplasia in the treated group. Gastric adenocarcinoma was seen in one rat (2%). No similar tumor was seen in male or female rats treated for two years. For this strain of rat no similar tumor has been noted historically, but a finding involving only one tumor is difficult to interpret. In a 52-week toxicity study in Sprague Dawley rats, brain astrocytomas were found in a small number of males that received omeprazole at dose levels of 0.4, 2, and 16 mg/kg/day (about 0.1 to 3.9 times the human dose of 40 mg/day on a body surface area basis). No astrocytomas were observed in female rats in this study. In a 2-year carcinogenicity study in Sprague Dawley rats, no astrocytomas were found in males and females at the high dose of 140.8 mg/kg/day (about 34 times the human dose of 40 mg/day on a body surface area basis). A 78-week mouse carcinogenicity study of omeprazole did not show increased tumor occurrence, but the study was not conclusive. A 26-week p53 (+/-) transgenic mouse carcinogenicity study was not positive.

Omeprazole was positive for clastogenic effects in an in vitro human lymphocyte chromosomal aberration assay, in one of two in vivo mouse micronucleus tests, and in an in vivo bone marrow cell chromosomal aberration assay. Omeprazole was negative in the in vitro Ames test, an in vitro mouse lymphoma cell forward mutation assay and an in vivo rat liver DNA damage assay.

In a 24-month carcinogenicity studies in rats, a dose-related significant increase in gastric carcinoid tumors and ECL cell hyperplasia was observed in both male and female animals [see Warnings and Precautions (5)]. Carcinoid tumors have also been observed in rats subjected to fundectomy or long-term treatment with other proton pump inhibitors or high doses of H2-receptor antagonists.

Omeprazole at oral doses up to 138 mg/kg/day (about 33.6 times the human dose of 40 mg/day on a body surface area basis) was found to have no effect on the fertility and general reproductive performance in rats.

13.2 Animal Toxicology and/or Pharmacology

Reproductive Toxicology Studies

Reproduction studies conducted in pregnant rats with omeprazole at doses up to 138 mg/kg/day (about 33.6 times an oral human dose of 40 mg on a body surface area basis) and in pregnant rabbits at doses up to 69 mg/kg/day (about 33.6 times an oral human dose of 40 mg on a body surface area basis) did not disclose any evidence for a teratogenic potential of omeprazole.

In rabbits, omeprazole in a dose range of 6.9 to 69 mg/kg/day (about 3.3 to 33.6 times the human dose of 40 mg/day on a body surface area basis) produced dose-related increases in embryo-lethality, fetal resorptions and pregnancy disruptions. In rats, dose-related embryo/fetal toxicity and postnatal developmental toxicity were observed in offspring resulting from parents treated with omeprazole at 13.8 to 138.0 mg/kg/day (about 3.3 to 33.6 times the human dose of 40 mg/day on a body surface area basis).

Juvenile Animal Study

A 28-day toxicity study with a 14-day recovery phase was conducted in juvenile rats with esomeprazole magnesium at doses of 70 to 280 mg /kg/day (about 17 to 68 times a daily oral human dose of 40 mg on a body surface area basis). An increase in the number of deaths at the high dose of 280 mg /kg/day was observed when juvenile rats were administered esomeprazole magnesium from postnatal day 7 through postnatal day 35. In addition, doses equal to or greater than 140 mg/kg/day (about 34 times a daily oral human dose of 40 mg on a body surface area basis), produced treatment-related decreases in body weight (approximately 14%) and body weight gain, decreases in femur weight and femur length, and affected overall growth. Comparable findings described above have also been observed in this study with another esomeprazole salt, esomeprazole strontium, at equimolar doses of esomeprazole.

14 CLINICAL STUDIES

14.1 Duodenal Ulcer Disease

Active Duodenal Ulcer – In a multicenter, double-blind, placebo controlled study of 147 patients with endoscopically documented duodenal ulcer, the percentage of patients healed (per protocol) at 2 and 4 weeks was significantly higher with omeprazole 20 mg once a day than with placebo (p ≤ 0.01). (See Table 6)

Table 5: Treatment of Active Duodenal Ulcer
% of Patients Healed
 | Omeprazole 20 mg a.m. (n=99) | Placebo a.m. (n=48)
Week 2 | 41 [(p ≤ 0.01)] | 13
Week 4 | 75 | 27

Complete daytime and nighttime pain relief occurred significantly faster (p ≤ 0.01) in patients treated with omeprazole 20 mg than in patients treated with placebo. At the end of the study, significantly more patients who had received omeprazole had complete relief of daytime pain (p ≤ 0.05) and nighttime pain (p ≤ 0.01).

In a multicenter, double-blind study of 293 patients with endoscopically documented duodenal ulcer, the percentage of patients healed (per protocol) at 4 weeks was significantly higher with omeprazole 20 mg once a day than with ranitidine 150 mg twice daily (p < 0.01). (See Table 7)

Table 6: Treatment of Active Duodenal Ulcer % of Patients Healed
 | Omeprazole 20 mg a.m. (n=145) | Ranitidine 150 mg twice daily (n=148)
Week 2 | 42 | 34
Week 4 | 82 [(p < 0.01)] | 63

Healing occurred significantly faster in patients treated with omeprazole than in those treated with ranitidine 150 mg twice daily (p < 0.01).

In a foreign multinational randomized, double-blind study of 105 patients with endoscopically documented duodenal ulcer, 40 mg and 20 mg of omeprazole were compared to 150 mg twice daily of ranitidine at 2, 4 and 8 weeks. At 2 and 4 weeks both doses of omeprazole were statistically superior (per protocol) to ranitidine, but 40 mg was not superior to 20 mg of omeprazole, and at 8 weeks there was no significant difference between any of the active drugs. (See Table 8)

Table : Treatment of Active Duodenal Ulcer % of Patients Healed
 | Omeprazole |  | Ranitidine 150 mg twice daily (n=35)
 | 40 mg (n=36) | 20 mg (n=34) | Ranitidine 150 mg twice daily (n=35)
Week 2 | 83 [(p ≤ 0.01)] | 83 | 53
Week 4 | 100 | 97 | 82
Week 8 | 100 | 100 | 94

14.2 Gastric Ulcer

In a U.S. multicenter, double-blind study of omeprazole 40 mg once a day, 20 mg once a day, and placebo in 520 patients with endoscopically diagnosed gastric ulcer, the following results were obtained. (See Table 9)

Table : Treatment of Gastric Ulcer % of Patients Healed (All Patients Treated)
 | Omeprazole 40 mg once daily (n=214) | Omeprazole 20 mg once daily (n=202) | Palcebo (n=104)
Week 4 | 55.6 [(p < 0.01) omeprazole 40 mg or 20 mg versus placebo] | 47.5 | 30.8
Week 8 | 82.7, [(p< 0.05) omeprazole 40 mg versus 20 mg] | 74.8 | 48.1

For the stratified groups of patients with ulcer size less than or equal to 1 cm, no difference in healing rates between 40 mg and 20 mg was detected at either 4 or 8 weeks. For patients with ulcer size greater than 1 cm, 40 mg was significantly more effective than 20 mg at 8 weeks.

In a foreign, multinational, double-blind study of 602 patients with endoscopically diagnosed gastric ulcer, omeprazole 40 mg once a day, 20 mg once a day, and ranitidine 150 mg twice a day were evaluated. (See Table 10)

Table 9: Treatment of Gastric Ulcer % of Patients Healed (All Patients Treated)
 | Omeprazole 40 mg once daily (n=187) | Omeprazole 20 mg once daily (n=200) | Ranitidine 150 mg twice daily (n=199)
Week 4 | 78.1 [(p < 0.01) omeprazole 40 versus ranitidine] , [(p< 0.01) omeprazole 40 mg versus 20 mg] | 63.5 | 56.3
Week 8 | 91.4, | 81.5 | 78.4

14.3 Gastroesophageal Reflux Disease (GERD)

Symptomatic GERD - A placebo controlled study was conducted in Scandinavia to compare the efficacy of omeprazole 20 mg or 10 mg once daily for up to 4 weeks in the treatment of heartburn and other symptoms in GERD patients without erosive esophagitis. Results are shown in Table 11.

Table 10: % Successful Symptomatic Outcome [Defined as complete resolution of heartburn]
 | Omeprazole 20 mg a.m. | Omeprazole 10 mg a.m. | Placebo a.m.
All patients | 46 [(p < 0.005) versus 10 mg] , [(p < 0.005) versus placebo] (n=205) | 31 (n=199) | 13 (n=105)
Patients with confirmed GERD | 56, (n=115) | 36 (n=109) | 14 (n=59)

Erosive Esophagitis - In a U.S. multicenter, double-blind, placebo controlled study of 40 mg or 20 mg of omeprazole delayed-release capsules in patients with symptoms of GERD and endoscopically diagnosed erosive esophagitis of grade 2 or above, the percentage healing rates (per protocol) were as shown in Table 12.

Table 11: % Patients Healed
 | Omeprazole 40 mg (n=87) | Omeprazole 20 mg (n=83) | Placebo (n=43)
Week 4 | 45 [(p < 0.01) Omeprazole versus placebo.] | 39 | 7
Week 8 | 75 | 74 | 14

In this study, the 40 mg dose was not superior to the 20 mg dose of omeprazole in the percentage healing rate. Other controlled clinical trials have also shown that omeprazole is effective in severe GERD. In comparisons with histamine H2-receptor antagonists in patients with erosive esophagitis, grade 2 or above, omeprazole in a dose of 20 mg was significantly more effective than the active controls. Complete daytime and nighttime heartburn relief occurred significantly faster (p < 0.01) in patients treated with omeprazole than in those taking placebo or histamine H2-receptor antagonists.

In this and five other controlled GERD studies, significantly more patients taking 20 mg omeprazole (84%) reported complete relief of GERD symptoms than patients receiving placebo (12%).

14.4 Long-Term Maintenance Treatment of Erosive Esophagitis

In a U.S. double-blind, randomized, multicenter, placebo-controlled study; two dose regimens of omeprazole were studied in patients with endoscopically confirmed healed esophagitis. Results to determine maintenance of healing of erosive esophagitis are shown in Table 13.

Table 12: Life Table Analysis
 | Omeprazole 20 mg once daily (n=138) | Omeprazole 20 mg 3 days per week (n=137) | Placebo (n=131)
Percent in endoscopic remission at 6 months | 70 [(p < 0.01) omeprazole 20 mg once daily versus omeprazole 20 mg 3 consecutive days per week or placebo.] | 34 | 11

In an international, multicenter, double-blind study, omeprazole 20 mg daily and 10 mg daily were compared to ranitidine 150 mg twice daily in patients with endoscopically confirmed healed esophagitis. Table 14 provides the results of this study for maintenance of healing of erosive esophagitis.

Table 13: Life Table Analysis
 | Omeprazole 20 mg once daily (n=131) | Omeprazole 10 mg once daily (n=133) | Ranitidine 150 mg twice daily (n=128)
Percent in Endoscopic Remission at 12 Months | 77 [(p = 0.01) omeprazole 20 mg once daily versus omeprazole 10 mg once daily or Ranitidine.] | 58 [(p = 0.03) omeprazole 10 mg once daily versus Ranitidine.] | 46

In patients who initially had grades 3 or 4 erosive esophagitis, for maintenance after healing 20 mg daily of omeprazole was effective, while 10 mg did not demonstrate effectiveness.

15 REFERENCES

1. Friedman JM and Polifka JE. Omeprazole. In: Teratogenic Effects of Drugs: A Resource for Clinicians (TERIS). 2nd ed. Baltimore, MD: The Johns Hopkins University Press 2000; p. 516.
2. Källén BA. Use of omeprazole during pregnancy – no hazard demonstrated in 955 infants exposed during pregnancy. Eur J Obstet Gynecol Reprod Biol 2001 May;96(1):63-8.
3. Ruigómez A, García Rodríquez LA, Cattaruzzi C, et al. Use of cimetidine, omeprazole, and ranitidine in pregnant women and pregnancy outcomes. Am J Epidemiol. 1999 Sep 1;150:476-81.
4. Lalkin A, Loebstein R, Addis A, et al. The safety of omeprazole during pregnancy: a multicenter prospective controlled study. Am J Obstet Gynecol. 1998 Sep 1:179 (3 Pt 1):727-30.

16 HOW SUPPLIED/STORAGE AND HANDLING

Omeprazole and Sodium Bicarbonate Capsules, 20mg/1100 mg: White to off white powder filled in size "00" hard gelatin capsules with opaque white colored cap and opaque white colored body imprinted "SG" on cap and "363" on body with black ink. They are supplied as:

NDC: 71205-984-30 Bottles of 30s

NDC: 71205-984-60 Bottles of 60s

NDC: 71205-984-90 Bottles of 90s

Omeprazole and Sodium Bicarbonate Capsules, 40 mg/1100 mg: White to off white powder filled in size "00" hard gelatin capsules with opaque light blue colored cap and opaque white colored body imprinted "SG" on cap and "364" on body with black ink. They are supplied as:

NDC: 71205-985-30 Bottles of 30s

NDC: 71205-985-60 Bottles of 60s

NDC: 71205-985-90 Bottles of 90s

Storage

Store at 25°C (77°F); excursions permitted to 15°C to 30°C (59°F to 86°F) [see USP Controlled Room Temperature].

Keep container tightly closed. Protect from light and moisture.

17 PATIENT COUNSELING INFORMATION

Advise the patient to read the FDA-approved patient labeling (Medication Guide).

Adverse Reactions

Advise patients to report to their healthcare provider if they experience any signs or symptoms consistent with:

- Hypersensitivity Reactions [see Contraindications (4)]
- Acute Interstitial Nephritis [see Warnings and Precautions (5.2)]
- Clostridium difficile-Associated Diarrhea [see Warnings and Precautions (5.4)]
- Bone Fracture [see Warnings and Precautions (5.5)]
- Cutaneous and Systemic Lupus Erythematosus [see Warnings and Precautions (5.6)]
- Cyanocobalamin (Vitamin B-12) Deficiency [see Warnings and Precautions (5.8)]
- Hypomagnesemia [see Warnings and Precautions (5.9)]

Sodium content

Patients on a sodium-restricted diet or patients at risk of developing congestive heart failure (CHF) should be informed of the sodium content of omeprazole and sodium bicarbonate capsules (304 mg per capsule). Patients should be informed that chronic use of sodium bicarbonate may cause problems and increased sodium intake can cause swelling and weight gain. If this occurs, they should contact their healthcare provider. [See Warnings and Precautions (5.3).]

Drug Interactions

Advise patients to report to their healthcare provider if they start treatment with clopidogrel, St. John's Wort or rifampin, or, if they take high-dose methotrexate. [see Warnings and Precautions (5.7, 5.10, 5.12)].

Administration

Instruct patients that omeprazole and sodium bicarbonate capsules should be taken on an empty stomach at least one hour prior to a meal. [See Dosage and Administration (2).]

Instruct patients in Directions for Use as follows:

Swallow intact capsule with water. DO NOT USE OTHER LIQUIDS. DO NOT OPEN CAPSULE AND SPRINKLE CONTENTS INTO FOOD.

Omeprazole and sodium bicarbonate is available either as 40 mg or 20 mg capsules with 1100 mg sodium bicarbonate.

Patients should be instructed not to substitute omeprazole and sodium bicarbonate capsules for other omeprazole and sodium bicarbonate dosage forms because different dosage forms contain different amounts of sodium bicarbonate and magnesium hydroxide. [See Dosage and Administration (2).]

Patients should be advised that since both the 20 mg and 40 mg capsules contain the same amount of sodium bicarbonate (1100 mg), two capsules of 20 mg are not equivalent to one capsule of omeprazole and sodium bicarbonate 40 mg; therefore, two 20 mg capsules of omeprazole and sodium bicarbonate should not be substituted for one capsule of omeprazole and sodium bicarbonate 40 mg. [See Dosage and Administration (2).]

Manufactured by:
ScieGen Pharmaceuticals, Inc.
Hauppauge, NY 11788 USA

Manufactured for:
Westminster Pharmaceuticals, LLC
Olive Branch, MS 38654 USA

Repackaged by:
Proficient Rx LP
Thousand Oaks, CA 91320

Rev: 07/18

MEDICATION GUIDE

Omeprazole and Sodium Bicarbonate Capsules
oh-ME-pray-zol/SO-dee-um by-KAR-boe-nate

Read this Medication Guide before you start taking omeprazole and sodium bicarbonate capsules and each time you get a refill. There may be new information. This information does not take the place of talking to your doctor about your medical condition or treatment.

What is the most important information I should know about Omeprazole and Sodium Bicarbonate Capsules?

Omeprazole and sodium bicarbonate capsules may help with your acid-related symptoms, but you could still have serious stomach problems. Talk with your doctor.

Omeprazole and sodium bicarbonate capsules can cause serious side effects, including:

- A type of kidney problem (acute interstitial nephritis). Some people who take proton pump inhibitor (PPI) medicines, including omeprazole and sodium bicarbonate capsules, may develop a kidney problem called acute interstitial nephritis that can happen at any time during treatment with omeprazole and sodium bicarbonate capsules. Call your doctor if you have a decrease in the amount that you urinate or if you have blood in your urine.
- Omeprazole and sodium bicarbonate capsules contains sodium bicarbonate. Tell your doctor if you are on a sodium restricted diet or if you have Bartter's Syndrome (a rare kidney disorder).
  Tell your doctor right away if you have confusion, shaking hands, dizziness, muscle twitching, nausea, vomiting, and numbness or tingling in the face, arms, or legs.
- Diarrhea. Omeprazole and sodium bicarbonate capsules may increase your risk of getting severe diarrhea. This diarrhea may be caused by an infection (Clostridium difficile) in your intestines.
  Call your doctor right away if you have watery stool, stomach pain, and fever that does not go away.
- Bone fractures. People who take multiple daily doses of PPI medicines for a long period of time (a year or longer) may have an increased risk of fractures of the hip, wrist or spine. You should take omeprazole and sodium bicarbonate capsules exactly as prescribed, at the lowest dose possible for your treatment and for the shortest time needed. Talk to your doctor about your risk of bone fracture if you take omeprazole and sodium bicarbonate capsules.
- Certain types of lupus erythematosus. Lupus erythematosus is an autoimmune disorder (the body's immune cells attack other cells or organs in the body). Some people who take PPI medicines, including omeprazole and sodium bicarbonate capsules, may develop certain types of lupus erythematosus or have worsening of the lupus they already have. Call your doctor right away if you have new or worsening joint paint or a rash on your cheeks or arms that gets worse in the sun.

Omeprazole and sodium bicarbonate capsules can have other serious side effects. See "Error! Hyperlink reference not valid."

What is Omeprazole and Sodium Bicarbonate Capsules?

Omeprazole and sodium bicarbonate capsules is a prescription medicine called a proton pump inhibitor (PPI). Omeprazole and sodium bicarbonate capsules reduces the amount of acid in your stomach.

Omeprazole and sodium bicarbonate capsules are used in adults:

- for 4 weeks to heal ulcers in the first part of the small bowel (duodenal ulcers). Your doctor may prescribe another 4 weeks of omeprazole and sodium bicarbonate capsules.
- for up to 8 weeks for healing stomach ulcers.
- for up to 4 weeks to treat heartburn and other symptoms that happen with gastroesophageal reflux disease (GERD).
  GERD happens when acid from the stomach backs up into the tube (esophagus) that connects your mouth to your stomach. This may cause a burning feeling in your chest or throat, sour taste, or burping.
- for up to 8 weeks to heal acid-related damage to the lining of the esophagus (called erosive esophagitis or EE).
- to maintain healing of the esophagus. It is not known if omeprazole and sodium bicarbonate capsules is safe and effective if used longer than 12 months (1 year).

It is not known if omeprazole and sodium bicarbonate is safe and effective in children less than 18 years of age.

Who should not take Omeprazole and Sodium Bicarbonate Capsules?

Do not take omeprazole and sodium bicarbonate capsules if you:

- are allergic to omeprazole or any of the ingredients in omeprazole and sodium bicarbonate capsules. See the end of this Medication Guide for a complete list of ingredients in omeprazole and sodium bicarbonate capsules.
- are allergic to any other proton pump inhibitor (PPI) medicine.

What should I tell my doctor before I take Omeprazole and Sodium Bicarbonate Capsules?

Before you take omeprazole and sodium bicarbonate capsules, tell your doctor if you:

- have been told that you have low magnesium, calcium, or potassium levels in your blood
- have liver problems
- have heart failure
- have Bartter's syndrome (a rare kidney disorder)
- have any allergies
- have any other medical conditions
- are pregnant or plan to become pregnant. It is not known if omeprazole and sodium bicarbonate can harm your unborn baby.
- are breastfeeding or plan to breastfeed. Omeprazole and sodium bicarbonate can pass into your breast milk and may harm your baby. You and your doctor should decide if you will take omeprazole and sodium bicarbonate capsules or breastfeed. You should not do both. Talk with your doctor about the best way to feed your baby if you take omeprazole and sodium bicarbonate capsules.

Tell your doctor about all the medicines you take, including prescription and non-prescription drugs, anti-cancer drugs, vitamins and herbal supplements. Omeprazole and sodium bicarbonate capsules may affect how other medicines work, and other medicines may affect how omeprazole and sodium bicarbonate capsules works.

Especially tell your doctor if you take:

- mycophenolate mofetil (Cellcept)
- diazepam (Valium)
- warfarin (Coumadin, Jantoven)
- phenytoin (Dilantin)
- cyclosporine (Gengraf, Neoral, Sandimmune)
- disulfiram (Antabuse)
- a benzodiazepine medicine
- ketoconazole (Nizoral)
- an antibiotic that contains ampicillin
- products that contain iron
- digoxin (Lanoxin)

- voriconazole (Vfend)
- atazanavir (Reyataz)
- nelfinavir (Viracept)
- tacrolimus (Prograf)
- saquinavir (Fortovase)
- clarithromycin (Biaxin, Biaxin XL)
- clopidogrel (Plavix)
- St. John's Wort (Hypericum perforatum)
- rifampin (Rifater, Rifamate, Rimactane, Rifadin)
- methotrexate

Ask your doctor or pharmacist for a list of these medicines, if you are not sure.

Know the medicines that you take. Keep a list of them to show your doctor and pharmacist when you get a new medicine.

How should I take Omeprazole and Sodium Bicarbonate Capsules?

- Take omeprazole and sodium bicarbonate capsules exactly as prescribed by your doctor.
- Do not change your dose or stop taking omeprazole and sodium bicarbonate capsules without talking to your doctor. Take omeprazole and sodium bicarbonate capsules on an empty stomach at least one hour before a meal.
- Swallow omeprazole and sodium bicarbonate capsules whole with water. Do not use other liquids. Do not crush or chew the capsule. Do not open the capsule and sprinkle contents into food.
- If you miss a dose of omeprazole and sodium bicarbonate capsules, take it as soon as you remember. If it is almost time for your next dose, do not take the missed dose. Take the next dose at your regular time. Do not take two doses to make up for a missed dose.
- Do not substitute two 20 mg capsules for one 40 mg capsule of omeprazole and sodium bicarbonate capsules because you will receive twice the amount of sodium bicarbonate. Talk to your doctor if you have questions.
- If you take too much omeprazole and sodium bicarbonate capsules, call your doctor or Poison Control Center right away, or go to the nearest hospital emergency room.
- Your doctor may prescribe antibiotic medicines with omeprazole and sodium bicarbonate capsules to help treat a stomach infection and heal stomach-area (duodenal) ulcers that are caused by bacteria called H. pylori. Make sure you read the patient information that comes with an antibiotic before you start taking it.

What are the possible side effects of Omeprazole and Sodium Bicarbonate Capsules?

Omeprazole and sodium bicarbonate capsules may cause serious side effects, including:

- See "Error! Hyperlink reference not valid."
- Vitamin B-12 deficiency. Omeprazole and sodium bicarbonate capsules reduces the amount of acid in your stomach. Stomach acid is needed to absorb vitamin B-12 properly. Talk with your doctor about the possibility of vitamin B-12 deficiency if you have been on omeprazole and sodium bicarbonate capsules for a long time (more than 3 years).
- Low magnesium levels in your body. This problem can be serious. Low magnesium can happen in some people who take a PPI medicine for at least 3 months. If low magnesium levels happen, it is usually after a year of treatment. You may or may not have symptoms of low magnesium.
  Tell your doctor right away if you develop any of these symptoms:

- seizures
- dizziness
- abnormal or fast heartbeat
- jitteriness
- jerking movements or shaking (tremors)

- muscle weakness
- spasms of the hands and feet
- cramps or muscle aches
- spasm of the voice box

Your doctor may check the level of magnesium in your body before you start taking omeprazole and sodium bicarbonate capsules, or during treatment, if you will be taking omeprazole and sodium bicarbonate capsules for a long period of time.

- Stomach growths (fundic gland polyps). People who take PPI medicines for a long time have an increased risk of developing a certain type of stomach growths called fundic gland polyps, especially after taking PPI medicines for more than 1 year. The most common side effects with omeprazole and sodium bicarbonate include:

- headache
- abdominal pain
- nausea

- diarrhea
- vomiting
- gas

Other side effects:

- Serious allergic reactions. Tell your doctor if you get any of the following symptoms with omeprazole and sodium bicarbonate capsules.

- rash
- face swelling

- throat tightness
- difficulty breathing

Your doctor may stop omeprazole and sodium bicarbonate capsules if these symptoms happen.

Using omeprazole and sodium bicarbonate capsules for a long time may cause problems such as swelling and weight gain. Tell your doctor if this happens.

If you are on a low-sodium diet or at risk of developing congestive heart failure (CHF), you and your doctor should decide if you will take omeprazole and sodium bicarbonate capsules.

Tell your doctor if you have any side effect that bothers you or that does not go away.

These are not all the possible side effects of omeprazole and sodium bicarbonate capsules. For more information, ask your doctor or pharmacist.

Call your doctor for medical advice about side effects. You may report side effects to FDA at 1-800-FDA-1088.

How should I store Omeprazole and Sodium Bicarbonate Capsules?

- Store omeprazole and sodium bicarbonate capsules at room temperature between 59°F to 86°F (15°C to 30°C).
- Keep omeprazole and sodium bicarbonate capsules in a tightly closed container.
- Keep omeprazole and sodium bicarbonate capsules in a dry place and out of light.

Keep omeprazole and sodium bicarbonate capsules and all medicines out of the reach of children.

General information about Omeprazole and Sodium Bicarbonate Capsules

Medicines are sometimes prescribed for purposes other than those listed in a Medication Guide. Do not use omeprazole and sodium bicarbonate capsules for any condition for which it was not prescribed by your doctor. Do not give omeprazole and sodium bicarbonate capsules to other people, even if they have the same symptoms as you. It may harm them.

This Medication Guide summarizes the most important information about omeprazole and sodium bicarbonate capsules. If you would like more information, talk to your doctor. You can also ask your doctor or pharmacist for information about omeprazole and sodium bicarbonate that is written for healthcare professionals.

For more information, call 1-844-221-7294.

What are the ingredients in Omeprazole and Sodium Bicarbonate Capsules?

Active ingredients: omeprazole, USP

Inactive ingredients of omeprazole and sodium bicarbonate capsules: sodium bicarbonate, croscarmellose sodium and sodium stearyl fumarate. The capsules consist of gelatin and titanium dioxide. In addition the 20 mg/1100 mg capsule shell contains sodium lauryl sulfate and the 40 mg/1100 mg capsule shell contains FD&C Blue 1. The capsules are printed with edible ink containing black iron oxide, butyl alcohol, dehydrated alcohol, isopropyl alcohol, propylene glycol, potassium hydroxide, shellac and strong ammonia solution.

Instructions for Use

For instructions on taking omeprazole and sodium bicarbonate capsules by mouth, see "Error! Hyperlink reference not valid."

This Medication Guide has been approved by the U.S. Food and Drug Administration.

Manufactured by:
ScieGen Pharmaceuticals, Inc.
Hauppauge, NY 11788 USA

Manufactured for:
Westminster Pharmaceuticals, LLC
Olive Branch, MS 38654 USA

Repackaged by:
Proficient Rx LP
Thousand Oaks, CA 91320

Rev: 07/18

PRINCIPAL DISPLAY PANEL - 20 mg Capsule Bottle Label

NDC 71205-984-60
Rx Only

Omeprazole and Sodium
Bicarbonate Capsules

20 mg/1100 mg

PHARMACIST: Dispense the accompanying
Medication Guide to each patient.

60 Capsules

PRINCIPAL DISPLAY PANEL - 40 mg Capsule Bottle Label

NDC 71205-985-60
Rx Only

Omeprazole and Sodium
Bicarbonate Capsules

40 mg/1100 mg

PHARMACIST: Dispense the accompanying
Medication Guide to each patient.

60 Capsules